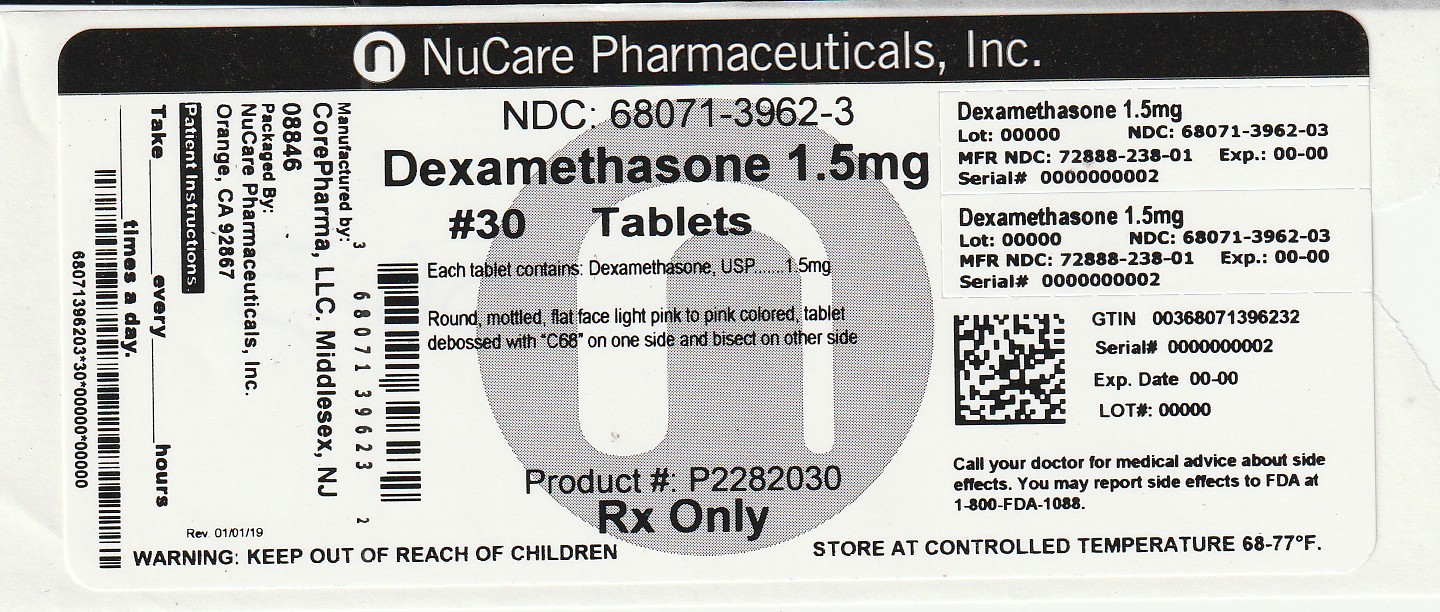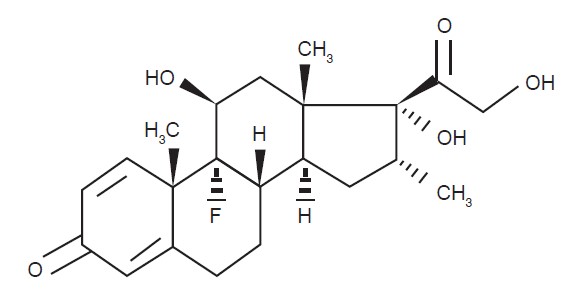 DRUG LABEL: DEXAMETHASONE
NDC: 68071-3962 | Form: TABLET
Manufacturer: NuCare Pharmaceuticals, Inc.
Category: prescription | Type: HUMAN PRESCRIPTION DRUG LABEL
Date: 20260210

ACTIVE INGREDIENTS: DEXAMETHASONE 1.5 mg/1 1
INACTIVE INGREDIENTS: STARCH, CORN; CROSCARMELLOSE SODIUM; ANHYDROUS LACTOSE; LACTOSE MONOHYDRATE; MAGNESIUM STEARATE; FD&C RED NO. 40; D&C RED NO. 27 ALUMINUM LAKE

Dexamethasone Tablets, USP
Rx only

Description

Dexamethasone Tablets, USP are available for oral administration containing either 0.5 mg, 0.75 mg, 1 mg, 1.5 mg, 2 mg, 4 mg or 6 mg of dexamethasone, USP. Each tablet contains the following inactive ingredients: Anhydrous lactose, corn starch, croscarmellose sodium, lactose monohydrate, magnesium stearate, D&C Yellow #10 Aluminum lake (0.5 mg and 4 mg), FD&C Blue #1 Aluminum lake (0.75 mg, 4 mg and 6 mg), FD&C Yellow #6 Aluminum lake (0.5 mg), FD&C Red #40 Aluminum lake (1.5 mg), D&C Red #27 Aluminum lake (1.5 mg), and Ferric Oxide Yellow (1 mg).

Dexamethasone, USP, a synthetic adrenocortical steroid, is a white or almost- white crystalline powder. It is stable in air. It is practically insoluble in water. The empirical formula is C22H29FO5. The molecular weight is 392.47 g/mol. It is designated chemically as (11β,16α)-9-fluoro-11,17,21-trihydroxy-16-methylpregna-1,4-diene-3,20-dione and the structural formula is:

Meets USP Dissolution Test 2.

CLINICAL PHARMACOLOGY

Glucocorticoids, naturally occurring and synthetic, are adrenocortical steroids that are readily absorbed from the gastrointestinal tract. Glucocorticoids cause varied metabolic effects. In addition, they modify the body's immune responses to diverse stimuli. Naturally occurring glucocorticoids (hydrocortisone and cortisone), which also have sodium-retaining properties, are used as replacement therapy in adrenocortical deficiency states. Their synthetic analogs including dexamethasone are primarily used for their anti-inflammatory effects in disorders of many organ systems.

At equipotent anti-inflammatory doses, dexamethasone almost completely lacks the sodium-retaining property of hydrocortisone and closely related derivatives of hydrocortisone.

INDICATIONS AND USAGE

Allergic States

Control of severe or incapacitating allergic conditions intractable to adequate trials of conventional treatment in asthma, atopic dermatitis, contact dermatitis, drug hypersensitivity reactions, perennial or seasonal allergic rhinitis, and serum sickness.

Dermatologic Diseases

Bullous dermatitis herpetiformis, exfoliative erythroderma, mycosis fungoides, pemphigus, and severe erythema multiforme (Stevens-Johnson syndrome).

Endocrine Disorders

Primary or secondary adrenocortical insufficiency (hydrocortisone or cortisone is the drug of choice; may be used in conjunction with synthetic mineralocorticoid analogs where applicable; in infancy mineralocorticoid supplementation is of particular importance), congenital adrenal hyperplasia, hypercalcemia associated with cancer, and nonsuppurative thyroiditis.

Gastrointestinal Diseases

To tide the patient over a critical period of the disease in regional enteritis and ulcerative colitis.

Hematologic Disorders

Acquired (autoimmune) hemolytic anemia, congenital (erythroid) hypoplastic anemia (Diamond-Blackfan anemia), idiopathic thrombocytopenic purpura in adults, pure red cell aplasia, and selected cases of secondary thrombocytopenia.

Miscellaneous

Diagnostic testing of adrenocortical hyperfunction, trichinosis with neurologic or myocardial involvement, tuberculous meningitis with subarachnoid block or impending block when used with appropriate antituberculous chemotherapy.

Neoplastic Diseases

For the palliative management of leukemias and lymphomas.

Nervous System

Acute exacerbations of multiple sclerosis, cerebral edema associated with primary or metastatic brain tumor, craniotomy, or head injury.

Ophthalmic Diseases

Sympathetic ophthalmia, temporal arteritis, uveitis, and ocular inflammatory conditions unresponsive to topical corticosteroids.

Renal Diseases

To induce a diuresis or remission of proteinuria in idiopathic nephrotic syndrome or that due to lupus erythematosus.

Respiratory Diseases

Berylliosis, fulminating or disseminated pulmonary tuberculosis when used concurrently with appropriate antituberculous chemotherapy, idiopathic eosinophilic pneumonias, symptomatic sarcoidosis.

Rheumatic Disorders

As adjunctive therapy for short-term administration (to tide the patient over an acute episode or exacerbation) in acute gouty arthritis, acute rheumatic carditis, ankylosing spondylitis, psoriatic arthritis, rheumatoid arthritis, including juvenile rheumatoid arthritis (selected cases may require low-dose maintenance therapy). For the treatment of dermatomyositis, polymyositis, and systemic lupus erythematosus.

CONTRAINDICATIONS

Systemic fungal infections (see WARNINGS, Fungal Infections). Dexamethasone tablets are contraindicated in patients who are hypersensitive to any components of this product.

WARNINGS

General

Rare instances of anaphylactoid reactions have occurred in patients receiving corticosteroid therapy (see ADVERSE REACTIONS).

Increased dosage of rapidly acting corticosteroids is indicated in patients on corticosteroid therapy subjected to any unusual stress before, during, and after the stressful situation.

Immunosuppression and Increased Risk of Infection

Corticosteroids, including dexamethasone, suppress the immune system and increase the risk of infection with any pathogen, including viral, bacterial, fungal, protozoan, or helminthic pathogens.

Corticosteroids can:

- Reduce resistance to new infections
- Exacerbate existing infections
- Increase the risk of disseminated infections
- Increase the risk of reactivation or exacerbation of latent infections
- Mask some signs of infection

Corticosteroid-associated infections can be mild but can be severe and at times fatal. The rate of infectious complications increases with increasing corticosteroid dosages.

Monitor for the development of infection and consider dexamethasone withdrawal or dosage reduction as needed.

Do not administer dexamethasone by an intraarticular, intrabursal, intratendinous, or intralesional route in the presence of acute local infection.

Tuberculosis

If dexamethasone is used to treat a condition in patients with latent tuberculosis or tuberculin reactivity, reactivation of tuberculosis may occur. Closely monitor such patients for reactivation.

During prolonged dexamethasone therapy, patients with latent tuberculosis or tuberculin reactivity should receive chemoprophylaxis.

Varicella Zoster and Measles Viral Infections

Varicella and measles can have a serious or even fatal course in nonimmune patients taking corticosteroids, including dexamethasone. In corticosteroid-treated patients who have not had these diseases or are nonimmune, particular care should be taken to avoid exposure to varicella and measles:

- If a dexamethasone-treated patient is exposed to varicella, prophylaxis with varicella zoster immune globulin may be indicated. If varicella develops, treatment with antiviral agents may be considered.
- If a dexamethasone-treated patient is exposed to measles, prophylaxis with immunoglobulin may be indicated.

Hepatitis B Virus Reactivation

Hepatitis B virus reactivation can occur in patients who are hepatitis B carriers treated with immunosuppressive dosages of corticosteroids, including dexamethasone. Reactivation can also occur infrequently in corticosteroid-treated patients who appear to have resolved hepatitis B infection.

Screen patients for hepatitis B infection before initiating immunosuppressive (e.g., prolonged) treatment with dexamethasone.

For patients who show evidence of hepatitis B infection, recommend consultation with physicians with expertise in managing hepatitis B regarding monitoring and consideration for hepatitis B antiviral therapy.

Fungal Infections

Corticosteroids, including dexamethasone, may exacerbate systemic fungal infections; therefore, avoid dexamethasone use in the presence of such infections unless dexamethasone is needed to control drug reactions. For patients on chronic dexamethasone therapy who develop systemic fungal infections, dexamethasone withdrawal or dosage reduction is recommended.

Amebiasis

Corticosteroids, including dexamethasone, may activate latent amebiasis. Therefore, it is recommended that latent amebiasis or active amebiasis be ruled out before initiating dexamethasone in patients who have spent time in the tropics or patients with unexplained diarrhea.

Strongyloides Infestation

Corticosteroids, including dexamethasone, should be used with great care in patients with known or suspected Strongyloides (threadworm) infestation. In such patients, corticosteroid-induced immunosuppression may lead to Strongyloides hyperinfection and dissemination with widespread larval migration, often accompanied by severe enterocolitis and potentially fatal gram-negative septicemia.

Cerebral Malaria

Avoid corticosteroids, including dexamethasone, in patients with cerebral malaria.

Vaccination

Administration of live or live, attenuated vaccines is contraindicated in patients receiving immunosuppressive doses of corticosteroids. Killed or inactivated vaccines may be administered.

However, the response to such vaccines cannot be predicted.

Immunization procedures may be undertaken in patients who are receiving corticosteroids as replacement therapy, e.g., for Addison’s disease.

Ophthalmic

Use of corticosteroids may produce posterior subcapsular cataracts, glaucoma with possible damage to the optic nerves, and may enhance the establishment of secondary ocular infections due to bacteria, fungi, or viruses. Consider referral to an ophthalmologist for patients who develop ocular symptoms or use corticosteroid-containing products for more than 6 weeks. The use of oral corticosteroids is not recommended in the treatment of optic neuritis and may lead to an increase in the risk of new episodes. Corticosteroids should not be used in active ocular herpes simplex.

Kaposi’s Sarcoma

Kaposi’s sarcoma has been reported to occur in patients receiving corticosteroid therapy, most often for chronic conditions.

Discontinuation of corticosteroids may result in clinical improvement of Kaposi’s sarcoma.

Cardio-Renal

Average and large doses of corticosteroids can cause elevation of blood pressure, sodium and water retention, and increased excretion of potassium. These effects are less likely to occur with the synthetic derivatives except when used in large doses. Dietary salt restriction and potassium supplementation may be necessary. All corticosteroids increase calcium excretion.

Literature reports suggest an apparent association between use of corticosteroids and left ventricular free wall rupture after a recent myocardial infarction; therefore, therapy with corticosteroids should be used with great caution in these patients.

Endocrine

Corticosteroids can produce reversible hypothalamic-pituitary adrenal (HPA) axis suppression with the potential for glucocorticosteroid insufficiency after withdrawal of treatment. Adrenocortical insufficiency may result from too rapid withdrawal of corticosteroids and may be minimized by gradual reduction of dosage. This type of relative insufficiency may persist for months after discontinuation of therapy; therefore, in any situation of stress occurring during that period, hormone therapy should be reinstituted.

If the patient is receiving steroids already, dosage may have to be increased.

Metabolic clearance of corticosteroids is decreased in hypothyroid patients and increased in hyperthyroid patients. Changes in thyroid status of the patient may necessitate adjustment in dosage.

PRECAUTIONS

General

The lowest possible dose of corticosteroids should be used to control the condition under treatment. When reduction in dosage is possible, the reduction should be gradual.

Since complications of treatment with corticosteroids are dependent on the size of the dose and the duration of treatment, a risk/benefit decision must be made in each individual case as to dose and duration of treatment and as to whether daily or intermittent therapy should be used.

Cardio-Renal

As sodium retention with resultant edema and potassium loss may occur in patients receiving corticosteroids, these agents should be used with caution in patients with congestive heart failure, hypertension, or renal insufficiency.

Endocrine

Drug-induced secondary adrenocortical insufficiency may be minimized by gradual reduction of dosage. This type of relative insufficiency may persist for months after discontinuation of therapy; therefore, in any situation of stress occurring during that period, hormone therapy should be reinstituted. Since mineralocorticoid secretion may be impaired, salt and/or a mineralocorticoid should be administered concurrently.

Gastrointestinal

Steroids should be used with caution in active or latent peptic ulcers, diverticulitis, fresh intestinal anastomoses, and nonspecific ulcerative colitis, since they may increase the risk of a perforation.

Signs of peritoneal irritation following gastrointestinal perforation in patients receiving corticosteroids may be minimal or absent.

There is an enhanced effect due to decreased metabolism of corticosteroids in patients with cirrhosis.

Musculoskeletal

Corticosteroids decrease bone formation and increase bone resorption both through their effect on calcium regulation (i.e. decreasing absorption and increasing excretion) and inhibition of osteoblast function. This, together with a decrease in the protein matrix of the bone secondary to an increase in protein catabolism, and reduced sex hormone production, may lead to inhibition of bone growth in pediatric patients and the development of osteoporosis at any age. Special consideration should be given to patients at increased risk of osteoporosis (e.g., postmenopausal women) before initiating corticosteroid therapy.

Neuro-Psychiatric

Although controlled clinical trials have shown corticosteroids to be effective in speeding the resolution of acute exacerbations of multiple sclerosis, they do not show that they affect the ultimate outcome or natural history of the disease. The studies do show that relatively high doses of corticosteroids are necessary to demonstrate a significant effect (see DOSAGE AND ADMINISTRATION).

An acute myopathy has been observed with the use of high doses of corticosteroids, most often occurring in patients with disorders of neuromuscular transmission (e.g., myasthenia gravis), or in patients receiving concomitant therapy with neuromuscular blocking drugs (e.g., pancuronium). This acute myopathy is generalized, may involve ocular and respiratory muscles, and may result in quadriparesis. Elevation of creatinine kinase may occur. Clinical improvement or recovery after stopping corticosteroids may require weeks to years.

Psychic derangements may appear when corticosteroids are used, ranging from euphoria, insomnia, mood swings, personality changes, and severe depression, to frank psychotic manifestations. Also, existing emotional instability or psychotic tendencies may be aggravated by corticosteroids.

Ophthalmic

Intraocular pressure may become elevated in some individuals. If steroid therapy is continued for more than 6 weeks, intraocular pressure should be monitored.

Information for Patients

Patients should be warned not to discontinue the use of corticosteroids abruptly or without medical supervision. As prolonged use may cause adrenal insufficiency and make patients dependent on corticosteroids, they should advise any medical attendants that they are taking corticosteroids and they should seek medical advice at once should they develop an acute illness including fever or other signs of infection. Following prolonged therapy, withdrawal of corticosteroids may result in symptoms of the corticosteroid withdrawal syndrome including myalgia, arthralgia, and malaise.

Persons who are on corticosteroids should be warned to avoid exposure to chickenpox or measles. Patients should also be advised that if they are exposed, medical advice should be sought without delay.

Drug Interactions

Aminoglutethimide: Aminoglutethimide may diminish adrenal suppression by corticosteroids.

Amphotericin B injection and potassium-depleting agents: When corticosteroids are administered concomitantly with potassium-depleting agents (e.g., amphotericin B, diuretics), patients should be observed closely for development of hypokalemia. In addition, there have been cases reported in which concomitant use of amphotericin B and hydrocortisone was followed by cardiac enlargement and congestive heart failure.

Antibiotics: Macrolide antibiotics have been reported to cause a significant decrease in corticosteroid clearance (see Drug Interactions, CYP 3A4 Inducers, CYP 3A4 Inhibitorsand CYP 3A4 Substrates).

Anticholinesterases: Concomitant use of anticholinesterase agents and corticosteroids may produce severe weakness in patients with myasthenia gravis. If possible, anticholinesterase agents should be withdrawn at least 24 hours before initiating corticosteroid therapy.

Anticoagulants, oral: Co-administration of corticosteroids and warfarin usually results in inhibition of response to warfarin, although there have been some conflicting reports. Therefore, coagulation indices should be monitored frequently to maintain the desired anticoagulant effect.

Antidiabetics: Because corticosteroids may increase blood glucose concentrations, dosage adjustments of antidiabetic agents may be required.

Antitubercular drugs: Serum concentrations of isoniazid may be decreased.

Cholestyramine: Cholestyramine may increase the clearance of corticosteroids.

Cyclosporine: Increased activity of both cyclosporine and corticosteroids may occur when the two are used concurrently. Convulsions have been reported with this concurrent use.

Dexamethasone suppression test (DST): False-negative results in the dexamethasone suppression test (DST) in patients being treated with indomethacin have been reported. Thus, results of the DST should be interpreted with caution in these patients.

Digitalis glycosides: Patients on digitalis glycosides may be at increased risk of arrhythmias due to hypokalemia.

Ephedrine: Ephedrine may enhance the metabolic clearance of corticosteroids, resulting in decreased blood levels and lessened physiologic activity, thus requiring an increase in corticosteroid dosage.

Estrogens, including oral contraceptives: Estrogens may decrease the hepatic metabolism of certain corticosteroids, thereby increasing their effect.

CYP 3A4 Inducers: Dexamethasone is metabolized by CYP 3A4. Drugs which induce cytochrome P450 3A4 (CYP 3A4) enzyme activity (e.g., barbiturates, phenytoin, carbamazepine, rifampin)may enhance the metabolism of corticosteroids and require that the dosage of the corticosteroid be increased.

CYP 3A4 Inhibitors: Concomitant administration of dexamethasone with erythromycin, a moderate CYP 3A4 inhibitor, has the potential to result in increased plasma concentrations of dexamethasone. Ketoconazole, a strong CYP3A4 inhibitor, has been reported to decrease the metabolism of certain corticosteroids by up to 60%, leading to increased risk of corticosteroid side effects. In addition, ketoconazole alone can inhibit adrenal corticosteroid synthesis and may cause adrenal insufficiency during corticosteroid withdrawal.

Co-administration with other drugs which strongly inhibit CYP 3A4 (e.g., itraconazole, clarithromycin, ritonavir, cobicistat-containing products)may lead to increased plasma concentrations of corticosteroids and potentially increase the risk for systemic corticosteroid side effects. Consider the benefit of co-administration versus the potential risk of systemic corticosteroid effects, in which case patients should be monitored for systemic corticosteroid side effects.

CYP 3A4 Substrates: Dexamethasone is a moderate inducer of CYP 3A4. Coadministration with other drugs that are metabolized by CYP 3A4 (e.g., indinavir, erythromycin)may increase their clearance, resulting in decreased plasma concentration.

Nonsteroidal Anti-Inflammatory Agents (NSAIDS): Concomitant use of aspirin (or other nonsteroidal anti-inflammatory agents) and corticosteroids increases the risk of gastrointestinal side effects. Aspirin should be used cautiously in conjunction with corticosteroids in hypoprothrombinemia. The clearance of salicylates may be increased with concurrent use of corticosteroids.

Phenytoin: In post-marketing experience, there have been reports of both increases and decreases in phenytoin levels with dexamethasone co-administration, leading to alterations in seizure control.

Skin Tests: Corticosteroids may suppress reactions to skin tests.

Thalidomide: Co-administration with thalidomide should be employed cautiously, as toxic epidermal necrolysis has been reported with concomitant use.

Vaccines: Patients on corticosteroid therapy may exhibit a diminished response to toxoids and live or inactivated vaccines due to inhibition of antibody response. Corticosteroids may also potentiate the replication of some organisms contained in live attenuated vaccines. Routine administration of vaccines or toxoids should be deferred until corticosteroid therapy is discontinued if possible (see WARNINGS: Infections: Vaccination).

Carcinogenesis, Mutagenesis, Impairment of Fertility

No adequate studies have been conducted in animals to determine whether corticosteroids have a potential for carcinogenesis or mutagenesis.

Steroids may increase or decrease motility and number of spermatozoa in some patients.

Pregnancy

Teratogenic Effects

Corticosteroids have been shown to be teratogenic in many species when given in doses equivalent to the human dose. Animal studies in which corticosteroids have been given to pregnant mice, rats, and rabbits have yielded an increased incidence of cleft palate in the offspring. There are no adequate and well-controlled studies in pregnant women. Corticosteroids should be used during pregnancy only if the potential benefit justifies the potential risk to the fetus. Infants born to mothers who have received substantial doses of corticosteroids during pregnancy should be carefully observed for signs of hypoadrenalism.

Nursing Mothers

Systemically administered corticosteroids appear in human milk and could suppress growth, interfere with endogenous corticosteroid production, or cause other untoward effects. Because of the potential for serious adverse reactions in nursing infants from corticosteroids, a decision should be made whether to discontinue nursing or to discontinue the drug, taking into account the importance of the drug to the mother.

Pediatric Use

The efficacy and safety of corticosteroids in the pediatric population are based on the well-established course of effect of corticosteroids, which is similar in pediatric and adult populations. Published studies provide evidence of efficacy and safety in pediatric patients for the treatment of nephrotic syndrome (patients > 2 years of age), and aggressive lymphomas and leukemias (patients > 1 month of age). Other indications for pediatric use of corticosteroids, e.g., severe asthma and wheezing, are based on adequate and well-controlled trials conducted in adults, on the premises that the course of the diseases and their pathophysiology are considered to be substantially similar in both populations.

The adverse effects of corticosteroids in pediatric patients are similar to those in adults (see ADVERSE REACTIONS). Like adults, pediatric patients should be carefully observed with frequent measurements of blood pressure, weight, height, intraocular pressure, and clinical evaluation for the presence of infection, psychosocial disturbances, thromboembolism, peptic ulcers, cataracts, and osteoporosis. Pediatric patients who are treated with corticosteroids by any route, including systemically administered corticosteroids, may experience a decrease in their growth velocity. This negative impact of corticosteroids on growth has been observed at low systemic doses and in the absence of laboratory evidence of hypothalamic-pituitary-adrenal (HPA) axis suppression (i.e., cosyntropin stimulation and basal cortisol plasma levels). Growth velocity may therefore be a more sensitive indicator of systemic corticosteroid exposure in pediatric patients than some commonly used tests of HPA axis function. The linear growth of pediatric patients treated with corticosteroids should be monitored, and the potential growth effects of prolonged treatment should be weighed against clinical benefits obtained and the availability of treatment alternatives. In order to minimize the potential growth effects of corticosteroids, pediatric patients should be titratedto the lowest effective dose.

Geriatric Use

Clinical studies did not include sufficient numbers of subjects aged 65 and over to determine whether they respond differently from younger subjects. Other reported clinical experience has not identified differences in responses between the elderly and younger patients. In general, dose selection for an elderly patient should be cautious, usually starting at the low end of the dosing range, reflecting the greater frequency of decreased hepatic, renal, or cardiac function, and of concomitant disease or other drug therapy. In particular, the increased risk of diabetes mellitus, fluid retention and hypertension in elderly patients treated with corticosteroids should be considered.

ADVERSE REACTIONS

(Listed alphabetically, under each subsection)

The following adverse reactions have been reported with dexamethasone or other corticosteroids:

Allergic Reactions

Anaphylactoid reaction, anaphylaxis, angioedema.

Cardiovascular

Bradycardia, cardiac arrest, cardiac arrhythmias, cardiac enlargement, circulatory collapse, congestive heart failure, fat embolism, hypertension, hypertrophic cardiomyopathy in premature infants, myocardial rupture following recent myocardial infarction (see WARNINGS: Cardio-Renal), edema, pulmonary edema, syncope, tachycardia, thromboembolism, thrombophlebitis, vasculitis.

Dermatologic

Acne, allergic dermatitis, dry scaly skin, ecchymoses and petechiae, erythema, impaired wound healing, increased sweating, rash, striae, suppression of reactions to skin tests, thin fragile skin, thinning scalp hair, urticaria.

Endocrine

Decreased carbohydrate and glucose tolerance, development of cushingoid state, hyperglycemia, glycosuria, hirsutism, hypertrichosis, increased requirements for insulin or oral hypoglycemic agents in diabetes, manifestations of latent diabetes mellitus, menstrual irregularities, secondary adrenocortical and pituitary unresponsiveness (particularly in times of stress, as in trauma, surgery, or illness), suppression of growth in pediatric patients.

Fluid and Electrolyte Disturbances

Congestive heart failure in susceptible patients, fluid retention, hypokalemic alkalosis, potassium loss, sodium retention, tumor lysis syndrome.

Gastrointestinal

Abdominal distention, elevation in serum liver enzyme levels (usually reversible upon discontinuation), hepatomegaly, increased appetite, nausea, pancreatitis, peptic ulcer with possible perforation and hemorrhage, perforation of the small and large intestine (particularly in patients with inflammatory bowel disease), ulcerative esophagitis.

Metabolic

Negative nitrogen balance due to protein catabolism.

Musculoskeletal

Aseptic necrosis of femoral and humeral heads, loss of muscle mass, muscle weakness, osteoporosis, pathologic fracture of long bones, steroid myopathy, tendon rupture, vertebral compression fractures.

Neurological/Psychiatric

Convulsions, depression, emotional instability, euphoria, headache, increased intracranial pressure with papilledema (pseudotumor cerebri) usually following discontinuation of treatment, insomnia, mood swings, neuritis, neuropathy, paresthesia, personality changes, psychic disorders, vertigo.

Ophthalmic

Exophthalmos, glaucoma, increased intraocular pressure, posterior subcapsular cataracts, vision blurred.

Other

Abnormal fat deposits, decreased resistance to infection, hiccups, increased or decreased motility and number of spermatozoa, malaise, moon face, weight gain.

OVERDOSAGE

Treatment of overdosage is by supportive and symptomatic therapy. In the case of acute overdosage, according to the patient’s condition, supportive therapy may include gastric lavage or emesis.

DOSAGE AND ADMINISTRATION

For Oral Administration

The initial dosage varies from 0.75 mg to 9 mg a day depending on the disease being treated.

It Should Be Emphasized That Dosage Requirements Are Variable And Must Be Individualized On The Basis Of The Disease Under Treatment And The Response Of The Patient.

After a favorable response is noted, the proper maintenance dosage should be determined by decreasing the initial drug dosage in small decrements at appropriate time intervals until the lowest dosage that maintains an adequate clinical response is reached.

Situations which may make dosage adjustments necessary are changes in clinical status secondary to remissions or exacerbations in the disease process, the patient’s individual drug responsiveness, and the effect of patient exposure to stressful situations not directly related to the disease entity under treatment. In this latter situation it may be necessary to increase the dosage of the corticosteroid for a period of time consistent with the patient’s condition. If after long-term therapy the drug is to be stopped, it is recommended that it be withdrawn gradually rather than abruptly.

In the treatment of acute exacerbations of multiple sclerosis, daily doses of 30 mg of dexamethasone for a week followed by 4 mg to 12 mg every other day for one month have been shown to be effective (see PRECAUTIONS: Neuro-Psychiatric).

In pediatric patients, the initial dose of dexamethasone may vary depending on the specific disease entity being treated. The range of initial doses is 0.02 mg to 0.3 mg/kg/day in three or four divided doses (0.6 mg to 9 mg/m^2bsa/day)

For the purpose of comparison, the following is the equivalent milligram dosage of the various corticosteroids:

Cortisone, 25 mg | Triamcinolone, 4 mg
Hydrocortisone, 20 mg | Paramethasone, 2 mg
Prednisolone, 5 mg | Betamethasone, 0.75 mg
Prednisone, 5 mg | Dexamethasone, 0.75 mg
Methylprednisolone, 4 mg

These dose relationships apply only to oral or intravenous administration of these compounds. When these substances or their derivatives are injected intramuscularly or into joint spaces, their relative properties may be greatly altered.

In acute, self-limited allergic disorders or acute exacerbations of chronic allergic disorders,the following dosage schedule combining parenteral and oral therapy is suggested:

Dexamethasone sodium phosphate injection, 4 mg per mL

First Day

1 or 2 mL, intramuscularly

Dexamethasone tablets, 0.75 mg

Second Day

4 tablets in two divided doses

Third Day

4 tablets in two divided doses

Fourth Day

2 tablets in two divided doses

Fifth Day

1 tablet

Sixth Day

1 tablet

Seventh Day

No treatment

Eighth Day

Follow-up visit

This schedule is designed to ensure adequate therapy during acute episodes, while minimizing the risk of overdosage in chronic cases.

In cerebral edema, dexamethasone sodium phosphate injection is generally administered initially in a dosage of 10 mg intravenously followed by 4 mg every six hours intramuscularly until the symptoms of cerebral edema subside. Response is usually noted within 12 to 24 hours and dosage may be reduced after two to four days and gradually discontinued over a period of five to seven days. For palliative management of patients with recurrent or inoperable brain tumors, maintenance therapy with either dexamethasone sodium phosphate injection or dexamethasone tablets in a dosage of 2 mg two or three times daily may be effective.

Dexamethasone Suppression Tests

1. Tests for Cushing’s syndrome Give 1 mg of dexamethasone orally at 11:00 p.m.

Blood is drawn for plasma cortisol determination at 8:00 a.m. the following morning. For greater accuracy, give 0.5 mg of dexamethasone orally every 6 hours for 48 hours. Twenty-four hour urine collections are made for determination of 17-hydroxycorticosteroid excretion.

2. Test to distinguish Cushing’s syndrome due to pituitary ACTH excess from Cushing’s syndrome due to other causes.

Give 2 mg of dexamethasone orally every 6 hours for 48 hours. Twenty-four hour urine collections are made for determination of 17-hydroxycorticosteroid excretion.

HOW SUPPLIED

Dexamethasone Tablets USP, 1.5 mg,are supplied as light pink to pink colored, mottled, round, uncoated, flat face tablets, debossed with “C68” on one side and bisect on other side. They are available as follows:

Bottles of 30 with child-resistant closure: NDC 68071-3962-3

Store and Dispense

Store at 20° to 25°C (68° to 77°F) [see USP Controlled Room Temperature].

Protect from moisture.

Dispense in a tight, light-resistant, child-resistant container as defined in the USP.

To report SUSPECTED ADVERSE REACTIONS, contact CorePharma, LLC. at 732-419-8800 or FDA at 1-800-FDA-1088 or www.fda.gov/medwatch.

Manufactured by:

CorePharma, LLC.
215 Wood Ave, Middlesex, NJ 08846

Distributed by:
Advagen Pharma Ltd.,
East Windsor, NJ 08520, USA

Rev. 07/2025
40374